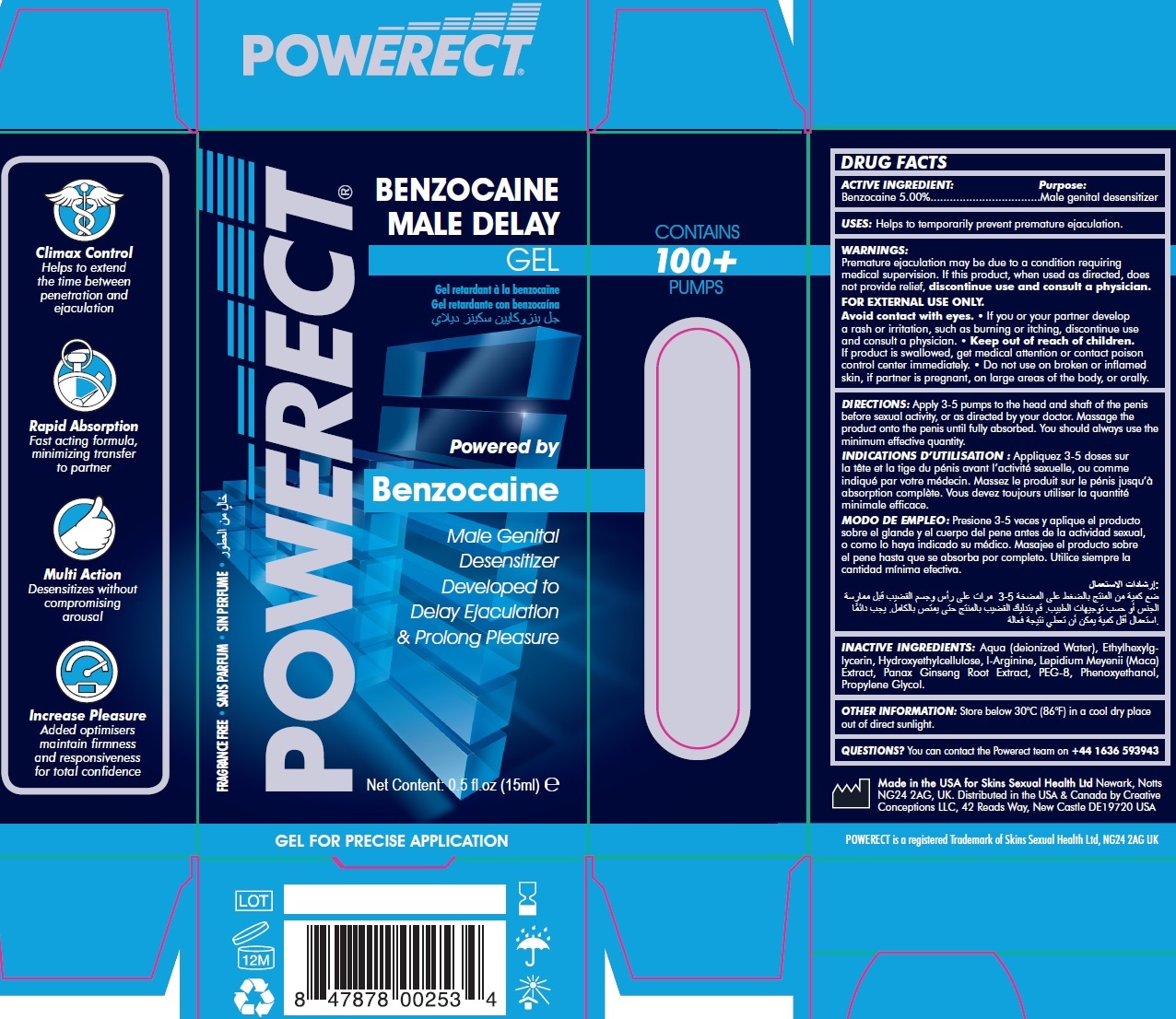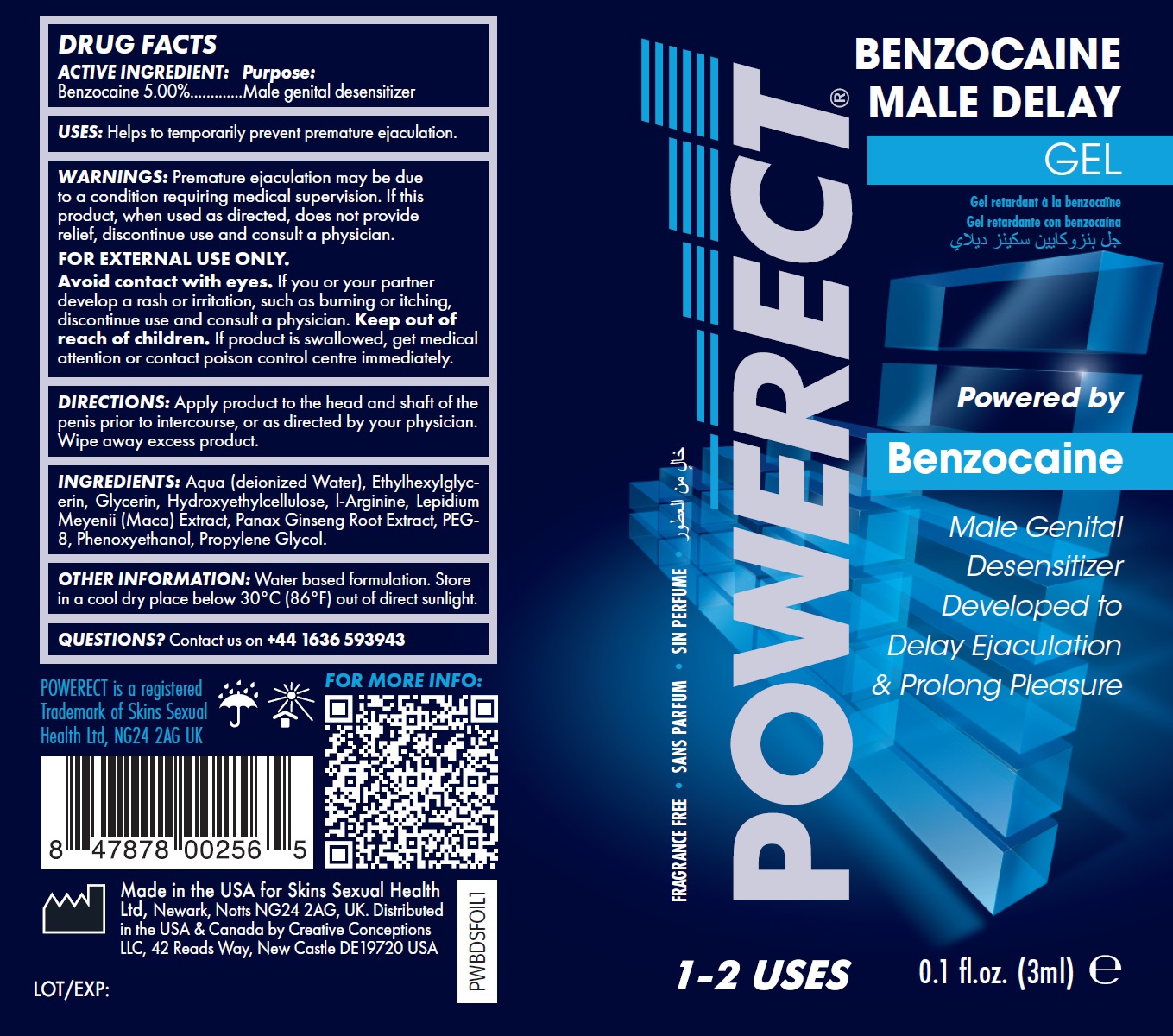 DRUG LABEL: POWERECT Benzocaine Male Delay Gel
NDC: 81923-367 | Form: GEL
Manufacturer: SKINS SEXUAL HEALTH LIMITED
Category: otc | Type: HUMAN OTC DRUG LABEL
Date: 20240716

ACTIVE INGREDIENTS: BENZOCAINE 50 mg/1 mL
INACTIVE INGREDIENTS: ALOE VERA LEAF; ETHYLHEXYLGLYCERIN; HYDROXYETHYL CELLULOSE, UNSPECIFIED; ARGININE; ASIAN GINSENG; POLYETHYLENE GLYCOL 400; PHENOXYETHANOL; PROPYLENE GLYCOL

POWERECT Benzocaine Male Delay Gel

ACTIVE INGREDIENT:

Benzocaine 5.00%

Purpose:

Male genital desensitizer

USES:

Helps to temporarily prevent premature ejaculation.

WARNINGS:

Premature ejaculation may be due to a condition requiring medical supervision. If this product, when used as directed, does not provide relief, discontinue use and consult a physician. If you or your partner develop a rash or irritation, such as burning or itching, discontinue use and consult a physician.
FOR EXTERNAL USE ONLY. Avoid contact with eyes.

Keep out of reach of children.

If product is swallowed, get medical attention or contact poison control center immediately.

DIRECTIONS:

Apply product to the head and shaft of the penis prior to intercourse, or as directed by your physician. Wipe away excess product.

INACTIVE INGREDIENTS:

Aqua (deionized Water), Ethylhexylglycerin, Hydroxyethylcellulose, l-Arginine, Lepidium Meyenii (Maca) Extract, Panax Ginseng Root Extract, PEG-8, Phenoxyethanol, Propylene Glycol.

OTHER INFORMATION:

Store in a cool dry place below 30°C (86°F) out of direct sunlight.

QUESTIONS?

Contact us on +44 1636 593943